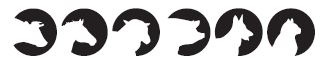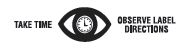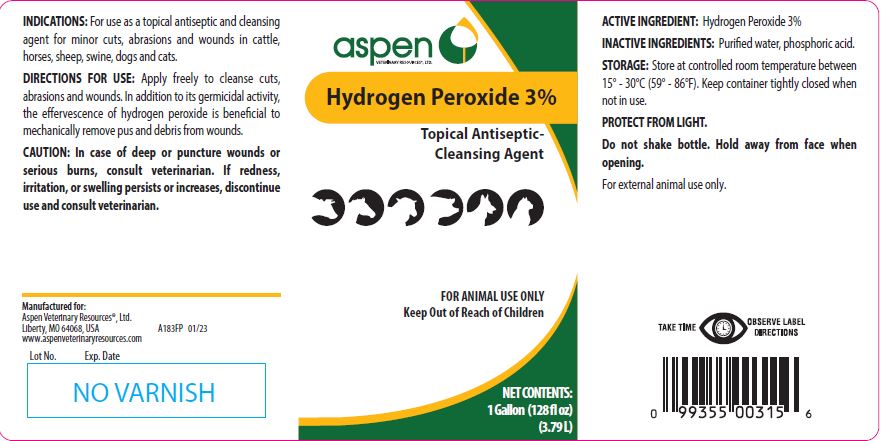 DRUG LABEL: Hydrogen Peroxide
NDC: 46066-229 | Form: SOLUTION
Manufacturer: Aspen Veterinary
Category: animal | Type: OTC ANIMAL DRUG LABEL
Date: 20230605

ACTIVE INGREDIENTS: HYDROGEN PEROXIDE 59.2 g/1 L

Hydrogen Peroxide 3% Solution

PURPOSE

Topical Antiseptic-Cleansing Agent

KEEP OUT OF REACH OF CHILDREN

FOR ANIMAL USE ONLY
Keep Out of Reach of Children

INDICATIONS:

For use as a topical antiseptic and cleansing agent for minor cuts, abrasions and wounds in cattle, horses, sheep, swine, dogs and cats.

DIRECTIONS FOR USE:

Apply freely to cleanse cuts, abrasions and wounds. In addition to its germicidal activity, the effervescence of hydrogen peroxide is beneficial to mechanically remove pus and debris from wounds.

CAUTION:

In case of deep or puncture wounds or serious burns, consult veterinarian. If redness, irritation, or swelling persists or increases, discontinue use and consult veterinarian.

ACTIVE INGREDIENT:

Hydrogen Peroxide 3%

STORAGE:

Store at controlled room temperature between 15° - 30°C (59° - 86°F). Keep container tightly closed when not in use.
PROTECT FROM LIGHT.

Do not shake bottle. Hold away from face when opening.
For external animal use only.

NET CONTENTS:

1 Gallon (128 fl oz) (3.79 L)

INFORMATION FOR OWNERS/CAREGIVERS

Manufactured for:

Aspen Veterinary Resources®, Ltd.
Liberty, MO 64068, USA A183FP 12/17
www.aspenveterinaryresources.com